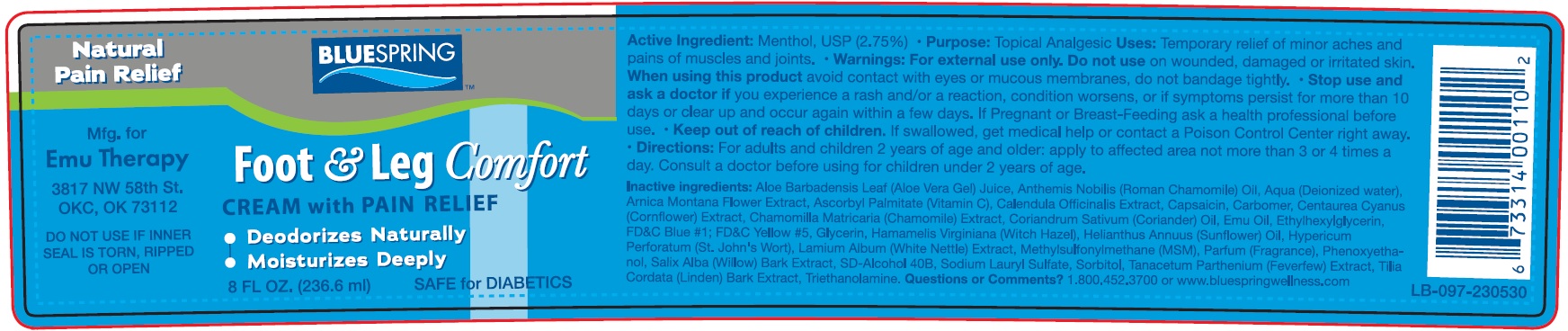 DRUG LABEL: BLUE SPRING Foot and Leg Comfort
NDC: 83591-418 | Form: CREAM
Manufacturer: ACA MANAGEMENT LLC
Category: otc | Type: HUMAN OTC DRUG LABEL
Date: 20231106

ACTIVE INGREDIENTS: MENTHOL 27.5 mg/1 mL
INACTIVE INGREDIENTS: HAMAMELIS VIRGINIANA ROOT BARK/STEM BARK; HYPERICUM PERFORATUM WHOLE; LAMIUM ALBUM WHOLE; DIMETHYL SULFONE; PHENOXYETHANOL; SALIX ALBA BARK; SODIUM LAURYL SULFATE; SORBITOL; FEVERFEW; TROLAMINE; ALOE VERA LEAF; WATER; ARNICA MONTANA FLOWER; ASCORBYL PALMITATE; CALENDULA OFFICINALIS FLOWER; CAPSAICIN; CARBOMER HOMOPOLYMER, UNSPECIFIED TYPE; CHAMOMILE; CORIANDER; EMU OIL; ETHYLHEXYLGLYCERIN; FD&C BLUE NO. 1; FD&C YELLOW NO. 5; GLYCERIN

BLUE SPRING Foot & Leg Comfort

Active Ingredient:

Menthol, USP (2.75%)

Purpose:

Topical Analgesic

Uses:

Temporary relief of minor aches and pains of muscles and joints.

Warnings:

- For external use only.

Do not use

on wounded, damaged or irritated skin.

When using this product

avoid contact with eyes or mucous membranes, do not bandage tightly.

Stop use and ask a doctor

- if you experience a rash and/or a reaction, condition worsens, or if symptoms persist for more than 10 days or clear up and occur again within a few days.

If pregnant or Breast-Feeding

- ask a health professional before use.

Keep out of reach of children.

If swallowed, get medical help or contact a Poison Control Center right away.

Directions:

- For adults and children 2 years of age and older: apply to affected area not more than 3 or 4 times a day. Consult a doctor before using for children under 2 years of age.

Inactive Ingredients:

Aloe Barbadensis leaf (Aloe Vera Gel) Juice, Anthemis Nobilis (Roman Chamomile) Oil, Aqua (Deionized water), Arnica Montana Flower Extract, Ascorbyl Palmitate (Vitamin C), Calendula Officinalis Extract, Capsaicin, Carbomer, Centaurea Cyanus (Cornflower) Extract, Chamomilla Matricaria (Chamomile) Extract, Coriandrum Sativum (Coriander) Oil, Emu Oil, Ethylhexylglycerin, FD&C Blue #1; FD&C Yellow #5, Glycerin, Hamamelis Virginiana (Witch Hazel), Helianthus Annuus (Sunflower) Oil, Hypericum Perforatum (St. John's Wort), Lamium Album (White Nettle) Extract, Methylsulfonylmethane (MSM), Parfum (Fragrance), Phenoxyethanol, Salix Alba (Willow) Bark Extract, SD-Alohol 40B, Sodium Lauryl Sulfate, Sorbitol, Tanacetum Parthenium (Feverfew) Extract, Tilla Cordata (Linden) Bark Extract, Triethanolamine.

Questions or Comments?

1-800-452-3700 or www.bluespringwellness.com